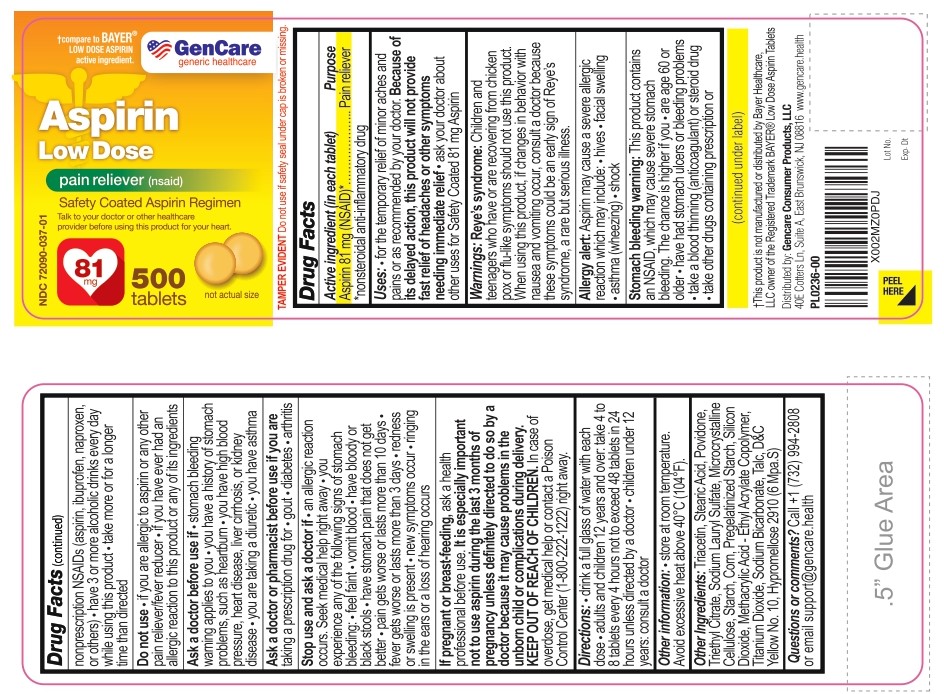 DRUG LABEL: Gencare-Aspirin Low Dose Pain reliever (NSAID)
NDC: 72090-037 | Form: TABLET
Manufacturer: Pioneer Life Sciences, LLC
Category: otc | Type: HUMAN OTC DRUG LABEL
Date: 20251226

ACTIVE INGREDIENTS: ASPIRIN 81 mg/1 1
INACTIVE INGREDIENTS: Triacetin; Stearic Acid; Povidone; Triethyl Citrate; Sodium Lauryl Sulfate; Microcrystalline Cellulose; STARCH, CORN; Silicon Dioxide; ETHYL ACRYLATE AND METHYL METHACRYLATE COPOLYMER (2:1; 600000 MW); Titanium Dioxide; Sodium Bicarbonate; Talc; D&C Yellow No. 10; HYPROMELLOSE 2910 (6 MPA.S)

Gencare-Aspirin Low Dose Pain reliever (NSAID)

Active Ingredient (in each tablet)

Aspirin 81mg (NSAID)*nonsteroidal anti-inflammatory drug

Purpose

Pain reliever

Uses:

• for the temporary relief of minor aches and pains or as recommended by your doctor. Because of its delayed action, this product will not provide fast relief of headaches or other symptoms needing immediate relief

• ask your doctor about other uses for Safety Coated 81 mg Aspirin

Warnings:

Reye's syndrome

Children and teenagers who have or are recovering from chickenpox or flu-like symptoms should not use this product. When using this product, if changes in behavior with nausea and vomiting occur, consult a doctor because these symptoms could be an early sign of Reye’s syndrome, a rare but serious illness.

Allergy alert

Aspirin may cause a severe allergic reaction which may include:

- hives
- facial swelling
- asthma (wheezing)
- shock

Stomach bleeding warning

This product contains an NSAID, which may cause severe stomach bleeding.

The chance is higher if you:

- are age 60 or older
- have had stomach ulcers or bleeding problems
- take a blood thinning (anticoagulant) or steroid drug
- take other drugs containing prescription or nonprescription NSAIDs (aspirin, ibuprofen, naproxen, or others)
- have 3 or more alcoholic drinks every day while using this product
- take more or for a longer time than directed

Do not use

- if you are allergic to aspirin or any other pain reliever/fever reducer
- if you have ever had an allergic reaction to this product or any of its ingredients

Ask a doctor before use if

- stomach bleeding warning applies to you
- you have a history of stomach problems, such as heartburn
- you have high blood pressure, heart disease, liver cirrhosis, or kidney disease
- you are taking a diuretic
- you have asthma

Ask a doctor or pharmacist before use if you are
taking a prescription drug for • gout • diabetes • arthritis

Stop use and ask a doctor if

- an allergic reaction occurs. Seek medical help right away
- you experiance any of the sollowing signs of
- stomoch bleeding
- feel faint
- vomit blood
- have bloody or black stools
- have stomach pain that does not get better
- pain gets worse or lasts more than 10 days
- fever gets worse or lasts more than 3 days
- redness or swelling is present
- new symptoms occur
- ringning in the ears or a loss of hearing occurs

PREGNANCY

If pregnant or breast-feeding,ask a health professional before use. It is especially important not to use aspirin during the last 3 months of pregnancy unless definitely directed to do so by a doctor because it may cause problems in the unborn child or complications during delivery.

KEEP OUT OF REACH OF CHILDREN

In case of overdose, get medical help or contact a Poison Control Center (1-800-222-1222) right away.

DIRECTIONS

- drink a full glass of water with each dose
- adults and children 12 years and over: take 4 to 8 tablets every 4 hours not to exceed 48 tablets in 24 hours unless directed by a doctor
- children under 12 years: consult a doctor

OTHER INFORMATION

• store at room temperature. Avoid excessive heat above 40°C (104°F).

INACTIVE INGREDIENTS

Triacetin, Stearic Acid, Povidone, Triethyl citrate, Sodium Lauryl Sulfate, Microcrystalline Cellulose, Starch Corn, Pregelatinized Starch, Silicon Dioxide, Methacrylic Acid - Ethyl Acrylate copolymer, Titanium Dioxide, Sodium Bicarbonate, Talc, D & C Yellow No. 10, Hypromellose 2910 (6 Mpa.S)

QUESTIONS OR COMMENTS?

Call +1-(732) 994-2808 or email support@gencare.health